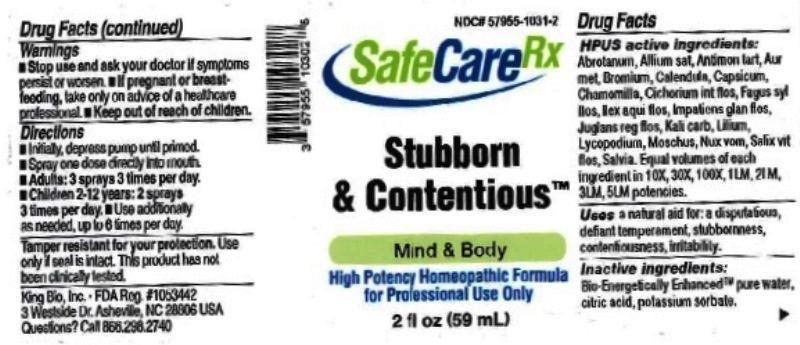 DRUG LABEL: Stubborn and Contentious
NDC: 57955-1031 | Form: LIQUID
Manufacturer: King Bio Inc.
Category: homeopathic | Type: HUMAN OTC DRUG LABEL
Date: 20161104

ACTIVE INGREDIENTS: ARTEMISIA ABROTANUM FLOWERING TOP 10 [hp_X]/59 mL; GARLIC 10 [hp_X]/59 mL; ANTIMONY POTASSIUM TARTRATE 10 [hp_X]/59 mL; GOLD 10 [hp_X]/59 mL; BROMINE 10 [hp_X]/59 mL; CALENDULA OFFICINALIS FLOWERING TOP 10 [hp_X]/59 mL; CAPSICUM 10 [hp_X]/59 mL; MATRICARIA RECUTITA 10 [hp_X]/59 mL; CICHORIUM INTYBUS FLOWER 10 [hp_X]/59 mL; FAGUS SYLVATICA FLOWERING TOP 10 [hp_X]/59 mL; ILEX AQUIFOLIUM FLOWERING TOP 10 [hp_X]/59 mL; IMPATIENS GLANDULIFERA FLOWER 10 [hp_X]/59 mL; JUGLANS REGIA FLOWERING TOP 10 [hp_X]/59 mL; POTASSIUM CARBONATE 10 [hp_X]/59 mL; LILIUM LANCIFOLIUM WHOLE FLOWERING 10 [hp_X]/59 mL; LYCOPODIUM CLAVATUM SPORE 10 [hp_X]/59 mL; MOSCHUS MOSCHIFERUS MUSK SAC RESIN 10 [hp_X]/59 mL; STRYCHNOS NUX-VOMICA SEED 10 [hp_X]/59 mL; SALIX ALBA FLOWERING TOP 10 [hp_X]/59 mL; SAGE 10 [hp_X]/59 mL
INACTIVE INGREDIENTS: WATER; ANHYDROUS CITRIC ACID; POTASSIUM SORBATE

Stubborn and Contentious™

ACTIVE INGREDIENT

Drug Facts__________________________________________________________________________________________________________

HPUS active ingredients: Abrotanum, Allium sativum, Antimonium tartaricum, Aurum metallicum, Bromium, Calendula officinalis, Capsicum annuum, Chamomilla, Cichorium intybus, flos, Fagus sylvatica, flos, Ilex aquifolium, flos, Impatiens glandulifera, flos, Juglans regia, flos, Kali carbonicum, Lilium tigrinum, Lycopodium clavatum, Moschus, Nux vomica, Salix vitellina, flos, Salvia officinalis. Equal volumes of each ingredient in 10X, 30X, 100X, 1LM, 2LM, 3LM, 5LM potencies.

INDICATIONS AND USAGE

Uses a natural aid for: a disputatious, defiant temperament, stubbornness, contentiousness, irritability.

Inactive Ingredients:

Bio-Energetically Enhanced™ pure water, citric acid and potassium sorbate.

Warnings

- Stop use and ask your doctor if symptoms persist or worsen.
- If pregnant or breast-feeding, take only on advice of a healthcare professional.

- Keep out of reach of children.

Directions

- Initially, depress pump until primed.
- Spray one dose directly into mouth.
- Adults: 3 sprays 3 times per day.
- Children 2-12: 2 sprays 3 times per day.
- Use additionally as needed, up to 6 times per day.

OTHER SAFETY INFORMATION

Tamper resistant for your protection. Use only if seal is intact. This product has not been clinically tested.

PURPOSE

Uses a natural aid for:

- a disputatious, defiant temperament
- stubbornness
- contentiousness
- irritability